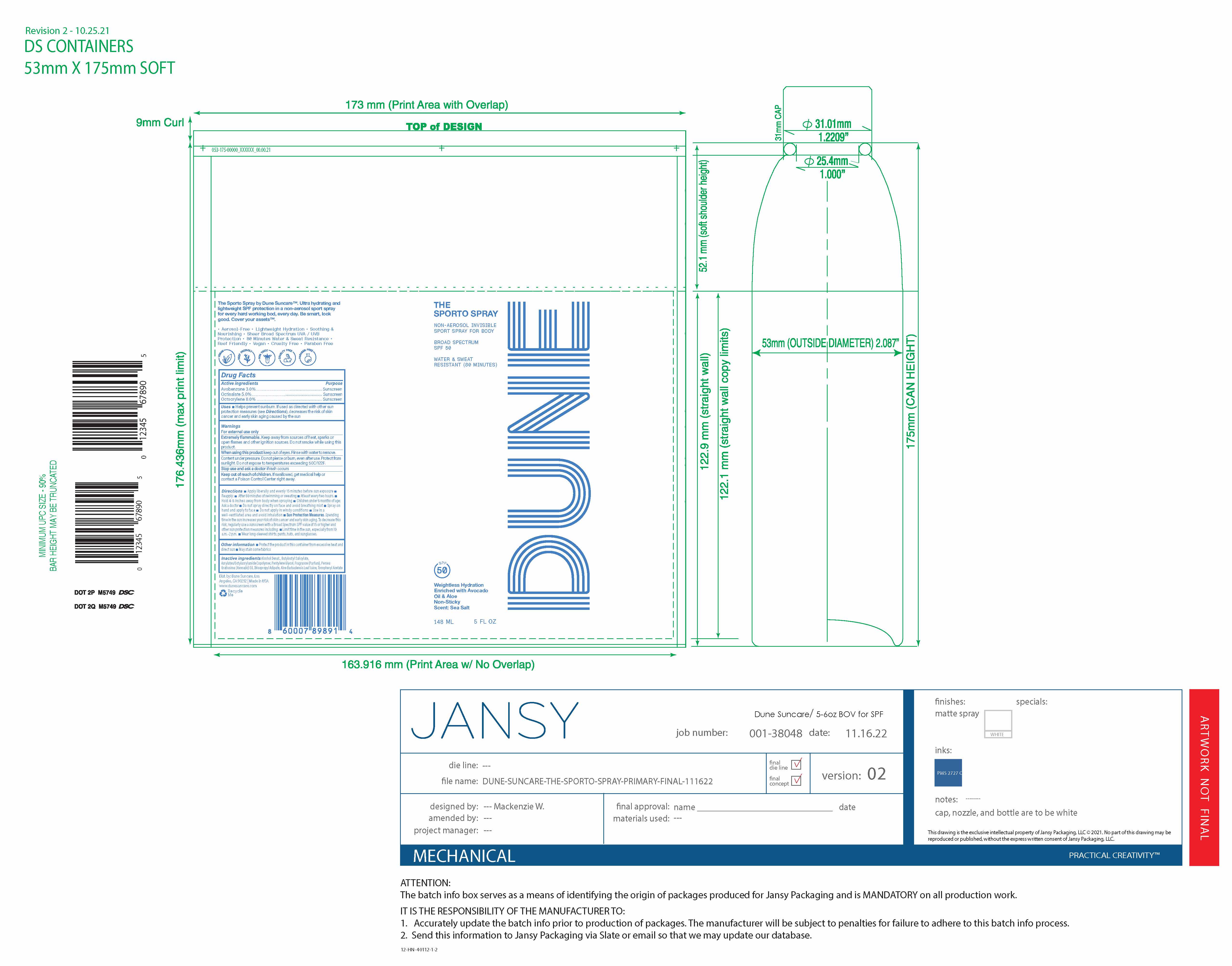 DRUG LABEL: THE SPORTO
NDC: 82757-204 | Form: SPRAY
Manufacturer: Dune Suncare, Inc.
Category: otc | Type: HUMAN OTC DRUG LABEL
Date: 20251219

ACTIVE INGREDIENTS: AVOBENZONE 30 mg/1 mL; OCTISALATE 50 mg/1 mL; OCTOCRYLENE 80 mg/1 mL
INACTIVE INGREDIENTS: ALOE BARBADENSIS LEAF JUICE; .ALPHA.-TOCOPHEROL ACETATE, D-; ALCOHOL; BUTYLOCTYL SALICYLATE; PERSEA GRATISSIMA (AVOCADO) OIL; DIISOPROPYL ADIPATE; PENTYLENE GLYCOL; FRAGRANCE 13576; ACRYLATES/OCTYLACRYLAMIDE COPOLYMER (40000 MW)

THE SPORTO SPRAY

Active Ingredients

Avobenzone 3.0%

Octisalate 5.0%

Octocrylene 8.0%

Purpose

Sunscreen

Uses

- helps prevent sunburn
- If used as directed with other sun protection measures (see Directions), decreases the risk of skin cancer and early skin aging caused by the sun

Warnings

For external use only

Extremely Flammable.

Keep away from sources of heat, sparks or open flames and other ingition sources. Do not smoke while using this product.

When using this product

keep out of eyes. Rinse with water to remove.

Contents under pressure.

Do not pierce or burn, even after use. Protect from sunlight. Do not expose to temperatures exceeding 50C/122F.

Stop use and ask a doctor

if rash occurs

Keep out of reach of children.

If swallowed, get medical help or contact a Poison Control Center right away.

Directions

- Apply liberally and evenly 15 minutes before sun exposure
- Reapply:
  - After 80 minutes of swimming or sweating
  - At least every two hours.
  - Hold 4-6 inches away from body when spraying
  - Children under 6 months: Ask a doctor
  - Do not spray directly on face and avoid breathing mist
  - Spray on head and apply to face
  - Do not apply in windy conditions
  - Use in a well-ventilated area and avoid inhalation
- Sun Protection Measures.Spending time in the sun increases your risk of skin cancer and early aging. To decrease this risk, regularly use a sunscreen with Broad Spectrum SPF value of 15 or higher and other sun protection measures including:
- limit time in the sun, especially from 10 a.m.–2 p.m.
- wear long-sleeve shirts, pants, hats, and sunglasses.

Other information

- Protect the product in this container from excessive heat and direct sun
- May stain some fabrics

Inactive ingredients

Alcohol Denat., Butyloctyl Salicylate, Acrylates/Octylacrylamide Copolymer, Pentylene Glycol, Fragrance (Parfum), Persea Gratissima (Avocado) Oil, Diisopropyl Adipate, Aloe Barbadensis Leaf Juice, Tocopheryl Acetate

Principal Display Panel

DUNE SUNCARE

THE SPORTO SPRAY

NON-AEROSOL INVISIBLE

SPORT SPRAY FOR

BODY

BROAD SPECTRUM

SPF 50

WATER & SWEAT

RESISTANT (80 MINUTES)

Weightless Hydration

Enriched with Avocado

Oil & Aloe

Non-Sticky

Scent: Sea Salt

148 mL

5 FL OZ